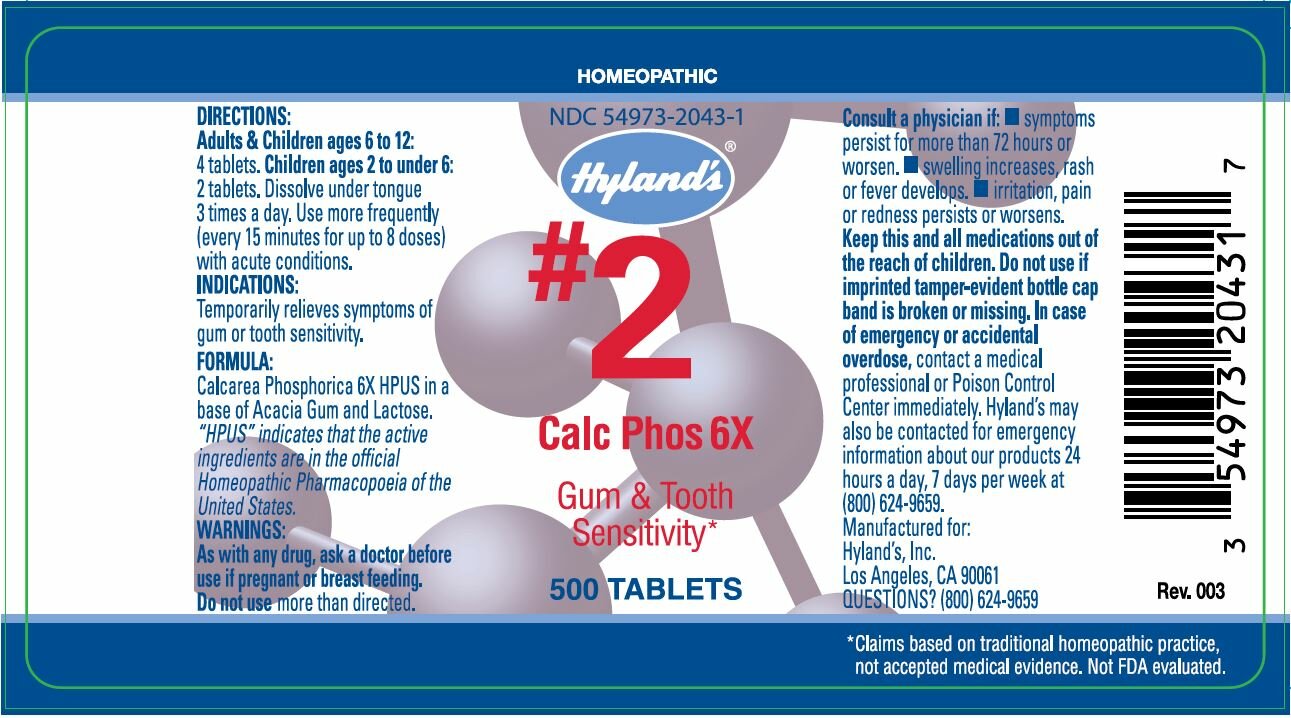 DRUG LABEL: CALC PHOS
NDC: 54973-2043 | Form: TABLET
Manufacturer: Hyland's Inc.
Category: homeopathic | Type: HUMAN OTC DRUG LABEL
Date: 20221207

ACTIVE INGREDIENTS: CALCIUM PHOSPHATE 6 [hp_X]/1 1
INACTIVE INGREDIENTS: LACTOSE; ACACIA

CALC PHOS 6X

DIRECTIONS

Adults & Children ages 6 - 12:

4 tablets.

Children ages 2 - 6:

2 tablets. Dissolve under tongue

3 times a day. Use more frequently

(every 15 minutes for up to 8 doses)

with acute conditions.

INDICATIONS

PURPOSE

Temporarily relieves symptoms of gum or tooth sensitivity.

FORMULA

Calcarea Phosphorica 6X HPUS

INACTIVE INGREDIENT

in a base of Acacia Gum, Lactose N.F.

"HPUS" indicates that the active

ingredients are in the official

Homeopathic Pharmacopœia of the

United States.

WARNINGS

PREGNANCY OR BREAST FEEDING

As with any drug, ask a doctor before use if pregnant or breast feeding.

Do not use more than directed.

Consult a physician if

- symptoms persist for more than 72 hours or worsen.
- swelling increases, rash or fever develops.
- irritation,pain or rednes persists or worsens.

KEEP OUT OF REACH OF CHILDREN

Keep this and all medications out of the reach of children.

Do not use if imprinted tamper-evident bottle cap band is broken or missing.

In case of an emergency or accidental overdose, contact a medical professional or Poison Control Center immediately. Hyland's may be contacted for emergency information about our products 24 hours, a day 7 days per week at (800) 624-9659.

QUESTIONS?

(800) 624-9659

PRINCIPAL DISPLAY PANEL - 500 Tablet Bottle Label

HOMEOPATHIC

NDC 54973-2043-01

Hyland's®

#2

Calc Phos 6X

Gum & Tooth

Sensitivity*

500 TABLETS